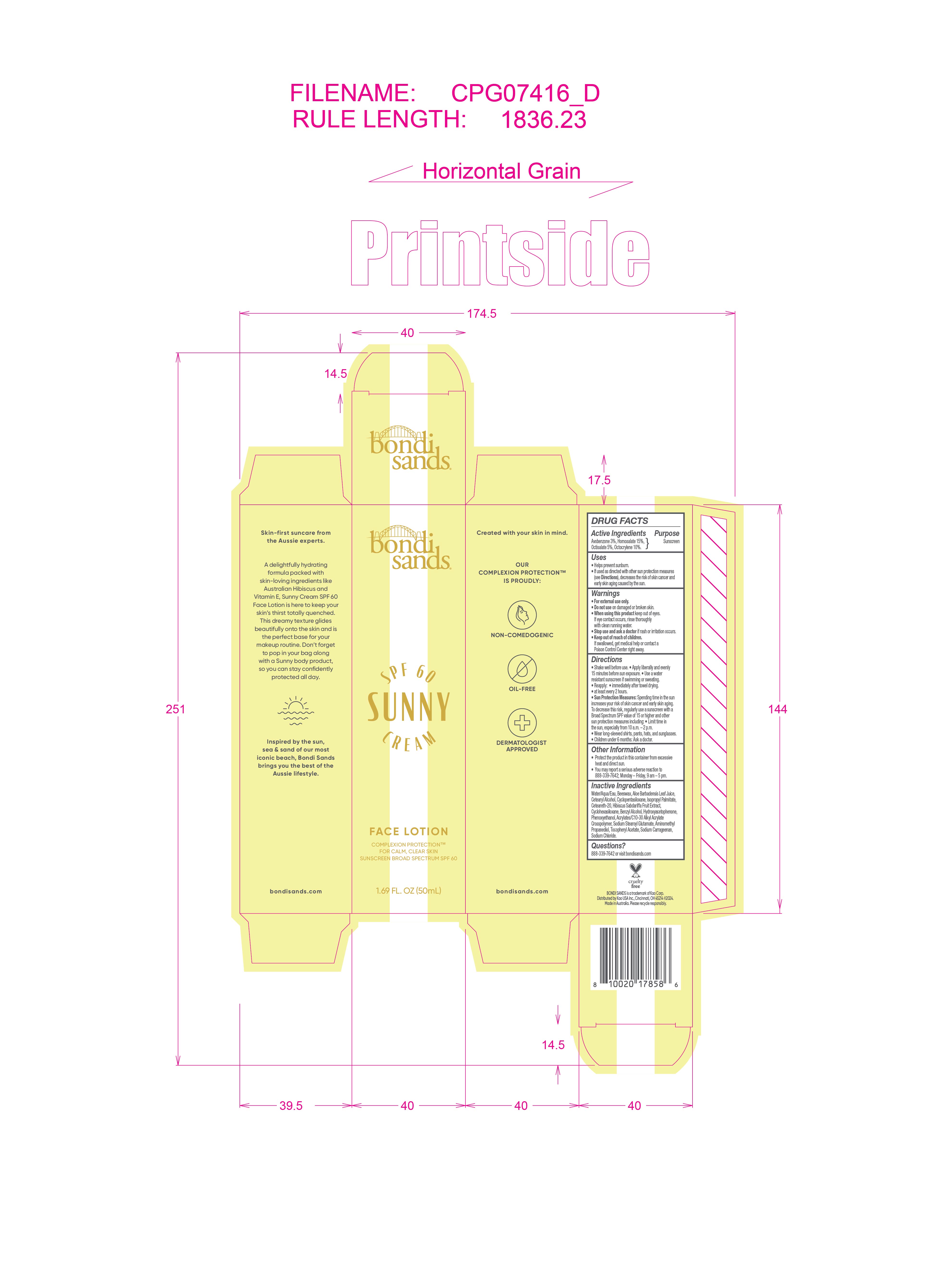 DRUG LABEL: Bondi Sands Broad Spectrum SPF 60 Sunny Cream Face
NDC: 70157-022 | Form: LOTION
Manufacturer: Baxter Laboratories Pty. Ltd.
Category: otc | Type: HUMAN OTC DRUG LABEL
Date: 20251107

ACTIVE INGREDIENTS: AVOBENZONE 3 g/100 mL; OCTOCRYLENE 10 g/100 mL; OCTISALATE 5 g/100 mL; HOMOSALATE 15 g/100 mL
INACTIVE INGREDIENTS: AMINOMETHYL PROPANEDIOL; CYCLOPENTASILOXANE; CYCLOHEXASILOXANE; PHENOXYETHANOL; CETEARETH-20; SODIUM CHLORIDE; ISOPROPYL PALMITATE; BENZYL ALCOHOL; HYDROXYACETOPHENONE; ACRYLATES/C10-30 ALKYL ACRYLATE CROSSPOLYMER (60000 MPA.S); SODIUM STEAROYL GLUTAMATE; .ALPHA.-TOCOPHEROL ACETATE; SODIUM CARRAGEENAN; BEESWAX; ALOE BARBADENSIS LEAF; WATER; CETEARYL ALCOHOL; HIBISCUS SABDARIFFA WHOLE

Bondi Sands Broad Spectrum SPF 60 Sunny Cream Face Lotion

Active Ingredients Purpose

Avobenzone 3%, Sunscreen

Homosalate15%

Octisalate 5%

Octocrylene 10%

Uses

- Helps prevent sunburn
- If used as directed with other sun protection measures (see Directions), decreases the risk of skin cancer and early skin aging caused by the sun

Keep out of reach of children. If swallowed, get medical help or contact a Poison Control Center right away.

Stop use and ask a doctor if rash or irritation occurs.

Warnings

- For external use only.
- Do not use on damaged or broken skin
- When using this product keep out of eyes. If eye contact occurs, rinse thoroughly with clean running water.

Directions

- Shake well before use
- Apply liberally 15 minutes before sun exposure.
- Use a water resistant sunscreen if swimming or sweating.
- Reapply :
- immediately after towel drying
- at least every 2 hours
- Sun Protection Measures. Spending time in the sun increases your risk of skin cancer and early skin aging. To decrease this risk, regularly use a sunscreen with a Broad Spectrum SPF value of 15 or higher and other sun protection measures including:

Limit time in the sun, especially from 10 a.m.- 2 p.m.

- Wear long-sleeved shirts, pants, hats, and sunglasses.
- Children under 6 months: Ask a doctor.

Other information

- Protect the product in this container from excessive heat anddirect sun
- You may report a serious adverse reaction to 888-339-7642; Monday - Friday , 9 am - 5 pm

Inactive Ingredients

Water/Aqua/Eau, Beeswax, Aloe Barbadensis Leaf Juice, Cetearyl Alcohol, Cyclopentasiloxane, Isopropyl Palmitate, Ceteareth-20,

Hibiscus Sabdariffa Fruit Extract, Cyclohexasiloxane, Benzyl Alcohol, Hydroxyacetopenone, Phenoxyethanol, Acrylates/C10-30 Alkyl Acrylate Crosspolymer, Sodium Stearoyl Glutamate, Aminomethyl Propanediol, Tocopheryl Acetate, Sodium Carrageenan, Sodium Chloride.

PACKAGE LABEL

bondi sands

SPF 60 Sunny Cream

Face Lotion

Sunscreen Broad Spectrum SPF 60

1.69 FL. OZ (50mL)